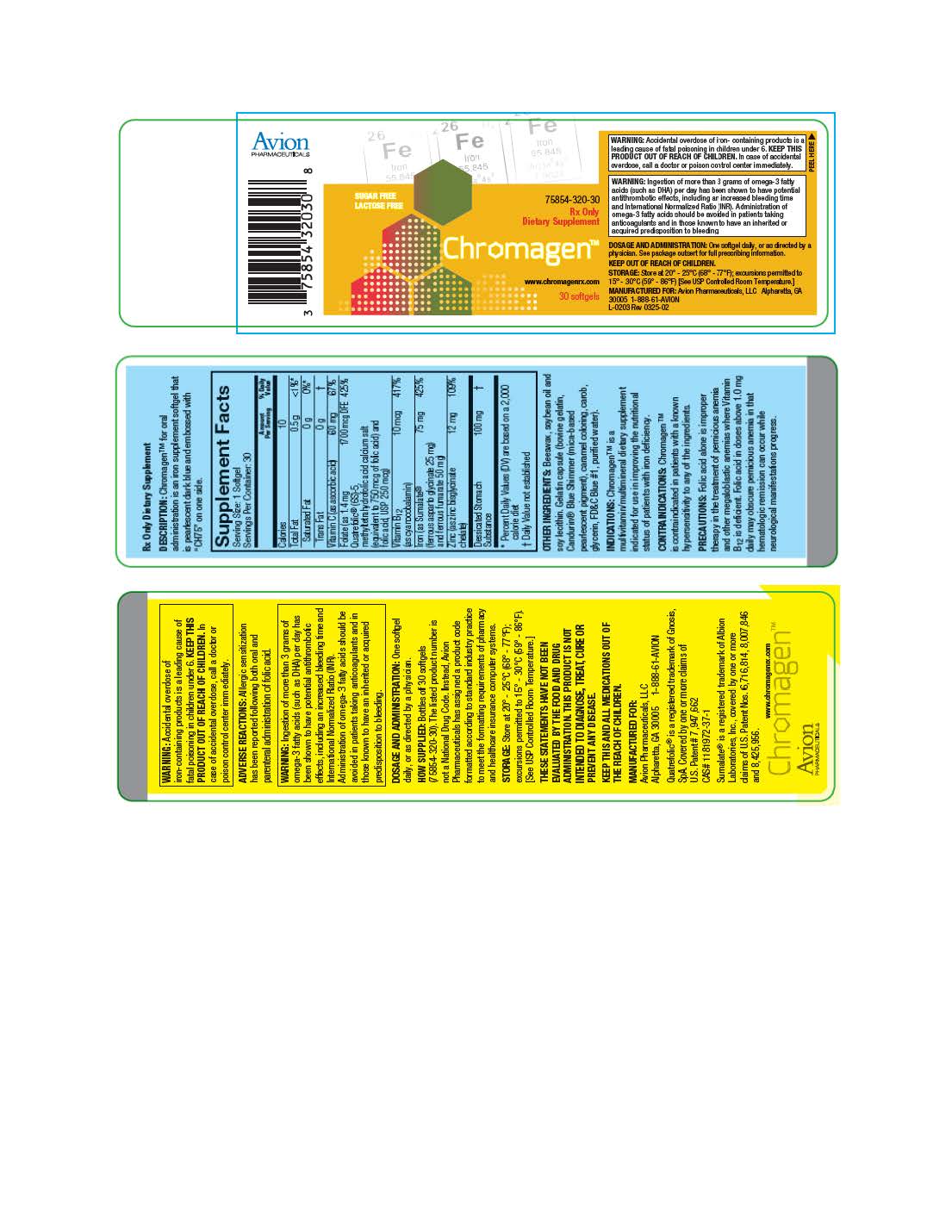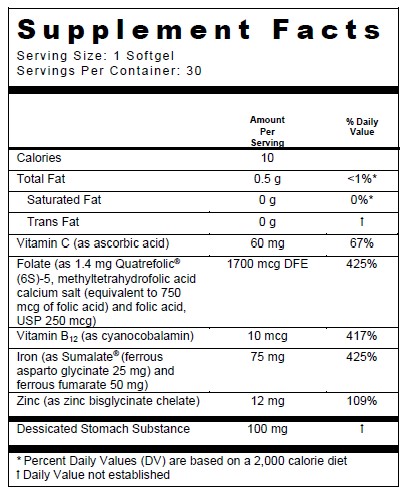 DRUG LABEL: Chromagen
NDC: 75854-320 | Form: CAPSULE
Manufacturer: Avion Pharmaceuticals, LLC
Category: prescription | Type: HUMAN PRESCRIPTION DRUG LABEL
Date: 20250410

ACTIVE INGREDIENTS: FERROUS ASPARTO GLYCINATE 25 mg/1 1; FERROUS FUMARATE 50 mg/1 1; ASCORBIC ACID 60 mg/1 1; LEVOMEFOLIC ACID 750 ug/1 1; FOLIC ACID 250 ug/1 1; CYANOCOBALAMIN 10 ug/1 1; ZINC 12 mg/1 1; INTRINSIC FACTOR 100 mg/1 1
INACTIVE INGREDIENTS: SOYBEAN OIL; GELATIN TYPE B BOVINE (200 BLOOM); GLYCERIN; WATER; CAROB; CARAMEL; FD&C BLUE NO. 1; YELLOW WAX; LECITHIN, SOYBEAN

Iron Supplement
ChromagenTM
Rx Only Dietary Supplement

DESCRIPTION

DESCRIPTION: Chromagen for oral administration is an iron supplement softgel that is pearlescent dark blue and embossed with CH75 on one side.

INACTIVE INGREDIENT

OTHER INGREDIENTS: Beeswax, soybean oil and soy lecithin. Gelatin capsule (bovine gelatin, Candurin® Blue Shimmer (mica-based pearlescent pigment), caramel coloring, carob, glycerin, FD&C Blue #1, purified water).

INDICATIONS AND USAGE

INDICATIONS: Chromagen™ is a multivitamin/multimineral dietary supplement indicated for use in improving the nutritional status of patients with iron deficiency.

CONTRAINDICATIONS

CONTRAINDICATIONS: Chromagen™ is contraindicated in patients with a known hypersensitivity to any of the ingredients.

PRECAUTIONS

PRECAUTIONS: Folic acid alone is improper therapy in the treatment of pernicious anemia and other megaloblastic anemias where Vitamin B12is deficient. Folic acid in doses above 1.0 mg daily may obscure pernicious anemia in that hematologic remission can occur while neurological manifestations progress.

BOXED WARNING

WARNING:Accidental overdose of iron-containing products is a leading cause of fatal poisoning in children under 6. KEEP THIS PRODUCT OUT OF REACH OF CHILDREN. In case of accidental overdose, call a doctor or poison control center immediately.

ADVERSE REACTIONS

ADVERSE REACTIONS:Allergic sensitization has been reported following both oral and parenteral administration of folic acid.

BOXED WARNING

WARNING:Ingestion of more than 3 grams of omega-3 fatty acids (such as DHA) per day has been shown to have potential antithrombotic effects, including an increased bleeding time and International Normalized Ratio (INR). Administration of omega-3 fatty acids should be avoided in patients taking anticoagulants and in those known to have an inherited or acquired predisposition to bleeding.

DOSAGE AND ADMINISTRATION:One softgel daily, or as directed by a physician.

HOW SUPPLIED

HOW SUPPLIED: Bottles of 30 softgels (75854-320-30). The listed product number is not a National Drug Code. Instead, Avion Pharmaceuticals has assigned a product code formatted according to standard industry practice to meet the formatting requirements of pharmacy and healthcare insurance computer systems.

STORAGE AND HANDLING

STORAGE:Store at 20° - 25°C (68° - 77°F); excursions permitted to 15° - 30°C (59° - 86°F) [See USP Controlled Room Temperature.]

KEEP THIS AND ALL MEDICATIONS OUT OFTHE REACH OF CHILDREN.

THESE STATEMENTS HAVE NOT BEEN EVALUATED BY THE FOOD AND DRUG ADMINISTRATION. THIS PRODUCT IS NOT INTENDED TO DIAGNOSE, TREAT, CURE OR PREVENT ANY DISEASE.

KEEP THIS AND ALL MEDICATIONS OUT OF THE REACH OF CHILDREN.

MANUFACTURED FOR:
Avion Pharmaceuticals, LLC
Alpharetta, GA 30005 1-888-61-AVION
L-0203 Rev. 0325-02

Quatrefolic® is a registered trademark of Gnosis, SpA. Covered by one or more claims of U.S. Patent # 7,947,662
CAS# 1181972-37-1

Sumalate® is a registered trademark of Albion Laboratories, Inc., covered by one or more claims of U.S. Patent Nos. 6,716,814,8,007,846 and 8,425, 956.

PACKAGE LABEL

75854-320-30

SUGAR FREE

LACTOSE FREE

Rx Only

Dietary Supplement

Chromagen™

30 softgels